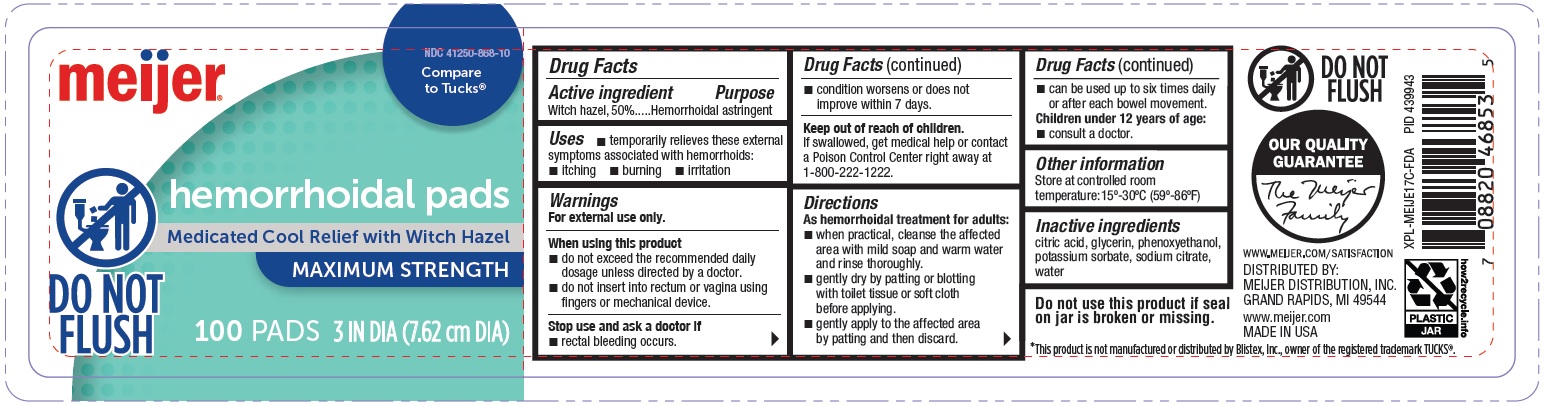 DRUG LABEL: hemorrhoidal pads
NDC: 41250-868 | Form: PATCH
Manufacturer: Meijer Distribution Inc.
Category: otc | Type: HUMAN OTC DRUG LABEL
Date: 20250711

ACTIVE INGREDIENTS: WITCH HAZEL 500 mg/1000 mg
INACTIVE INGREDIENTS: WATER; SODIUM CITRATE; CITRIC ACID MONOHYDRATE; GLYCERIN; PHENOXYETHANOL; POTASSIUM SORBATE

Drug Facts

Active Ingredient

Witch Hazel 50%

Purpose

Hemorrhoidal Astringent

Uses

Temporarily relieves these external symptoms associated with hemorrhoids:

- itching
- burning
- irritation

Warnings

For external rectal use only.

When using this product

- do not exceed the recommended daily dosage unless directed by a doctor.
- do not insert into rectum or vagina using fingers or mechanical device.

Stop use and ask a doctor if

- rectal bleeding occurs
- condition worsens or does not improve within 7 days.

Keep out of reach of children.

If swallowed, get medical help or contact a Poison Control Center right away at 1-800-222-1222.

Directions

As hemorrhoidal treatment for adults:

- when practical, cleanse the affected area with mild soap and warm water and rinse thoroughly.
- gently dry by patting or blotting with toilet tissue or soft cloth before applying.
- gently apply to the affected area by patting and then discard.
- can be used up to six times daily or after each bowel movement.

Children under 12 years of age

- consult a doctor.

Other Information

Store at controlled room temperature: 15º-30ºC (59º-86ºF)

Inactive Ingredients

Water, Sodium citrate, Citric acid, Glycerin, Phenoxyethanol, Potassium sorbate

Do not use this product if seal on jar is broken or missing.

* This product is not manufactured or distributed by Blistex, Inc., owner of the registered trademark TUCKS®.

Principal Display Panel

NDC 41250-868-10

meijer

Compare to Tucks

hemorrhoidal pads

Medicated Cool Relief with Witch Hazel

MAXIMUM STRENGTH

100 PADS 3 IN DIA (7.62 cm DIA)

DO NOT FLUSH